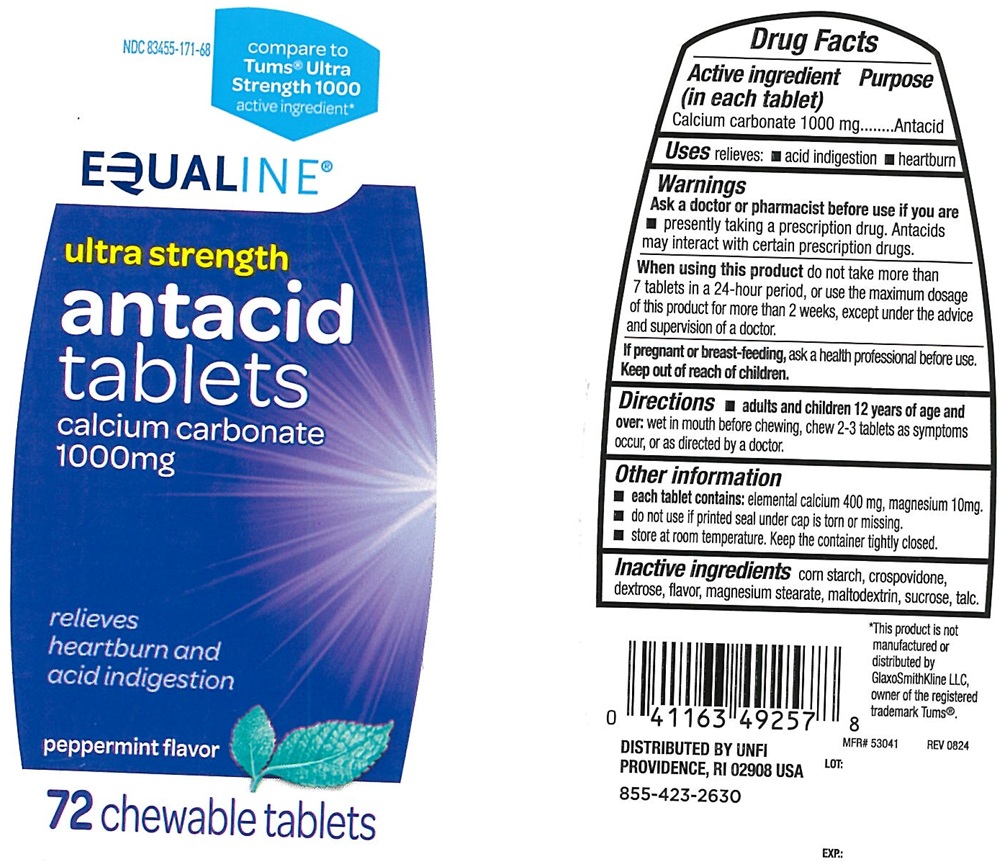 DRUG LABEL: Ultra Strength Antacid
NDC: 83455-171 | Form: TABLET, CHEWABLE
Manufacturer: UNITED NATURAL FOODS, INC. DBA UNFI
Category: otc | Type: Human OTC Drug Label
Date: 20250207

ACTIVE INGREDIENTS: CALCIUM CARBONATE 1000 mg/1 1
INACTIVE INGREDIENTS: STARCH, CORN; CROSPOVIDONE, UNSPECIFIED; DEXTROSE, UNSPECIFIED FORM; MAGNESIUM STEARATE; MALTODEXTRIN; SUCROSE; TALC

Ultra Strength Peppermint Antacid

ACTIVE INGREDIENT (in each tablet)

Calcium carbonate 1000 mg

PURPOSE

Antacid

USE(S)

relieves:

- acid indigestion
- heartburn

WARNINGS

.

ASK A DOCTOR OR PHARMACIST BEFORE USE IF YOU ARE

- presently taking a prescription drug. Antacids may interact with certain prescription drugs.

WHEN USING THIS PRODUCT

do not take more than 7 tablets in a 24-hour period, or use the maximum dosage of this product for more than 2 weeks, except under the advice and supervision of a doctor.

IF PREGNANT OR/BREASTFEEDING,

ask a health professional before use.

KEEP OUT OF REACH OF CHILDREN

.

DIRECTIONS

- adults and children 12 years of age and over: wet in mouth before chewing, chew 2-3 tablets as symptoms occur, or as directed by a doctor.

OTHER INFORMATION

- each tablet contains: elemental calcium 400 mg, magnesium 10 mg
- do not use if printed seal under cap is torn or missing
- store at room temperature. keep the container tightly closed.

INACTIVE INGREDIENTS

corn starch, crospovidone, dextrose, flavors, magnesium stearate, maltodextrin, sucrose, talc.

PRINCIPAL DISPLAY PANEL

NDC 83455-171-68

Compare to Tums® Ultra Strength 1000 active ingredient*

EQUALINE®

ultra strength
antacid tablets
calcium carbonate

1000 mg

Relieves

heartburn and

acid Indigestion

Peppermint flavor

72 chewable tablets